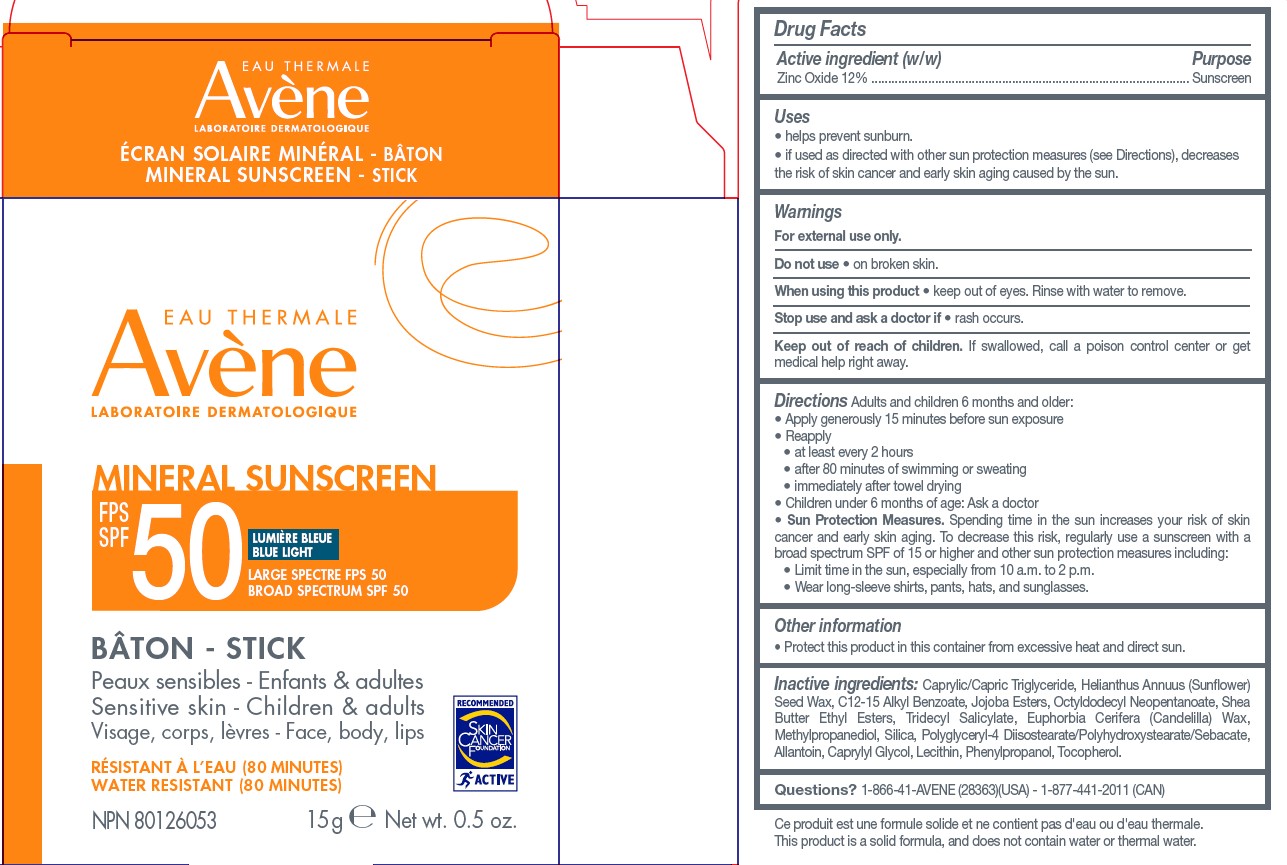 DRUG LABEL: Avene Mineral Sunscreen Stick SPF 50
NDC: 64760-784 | Form: STICK
Manufacturer: Pierre Fabre USA Inc.
Category: otc | Type: HUMAN OTC DRUG LABEL
Date: 20240311

ACTIVE INGREDIENTS: ZINC OXIDE 12 g/100 g
INACTIVE INGREDIENTS: MEDIUM-CHAIN TRIGLYCERIDES; OCTYLDODECYL NEOPENTANOATE; LECITHIN, SOYBEAN; PHENYLPROPANOL; HELIANTHUS ANNUUS SEED WAX; SILICON DIOXIDE; CAPRYLYL GLYCOL; ALKYL (C12-15) BENZOATE; TOCOPHEROL; JOJOBA OIL, RANDOMIZED; SHEA BUTTER ETHYL ESTERS; TRIDECYL SALICYLATE; CANDELILLA WAX; METHYLPROPANEDIOL; POLYGLYCERYL-4 DIISOSTEARATE/POLYHYDROXYSTEARATE/SEBACATE; ALLANTOIN

Avene Mineral Stick SPF 50

Active ingredient

Zinc oxide 12%

Purpose

Sunscreen

Uses

• helps prevent sunburn.
• if used as directed with other sun protection measures (see Directions), decreases the risk of skin cancer and early skin aging caused by the sun.

Warnings

For external use only.

Do not use

• on broken skin.

When using this product

• keep out of eyes. Rinse with water to remove.

Stop use and ask a doctor if

• rash occurs.

Keep out of reach of children

If swallowed, call a poison control center or get medical help right away.

Directions

Adults and children 6 months and older:

• Apply generously 15 minutes before sun exposure

• Reapply:

• at least every 2 hours

• after 80 minutes of swimming or sweating

• immediately after towel drying

• Children under 6 months of age: Ask a doctor

• Sun Protection Measures. Spending time in the sun increases your risk of skin cancer and early skin aging. To decrease this risk, regularly use a sunscreen with a broad spectrum SPF value of 15 or higher and other sun protection measures including: • Limit time in the sun, especially from 10 a.m. to 2 p.m. • Wear long-sleeve shirts, pants, hats, and sunglasses.

Other Information

• Protect this product in this container from excessive heat and direct sun.

Inactive Ingredients

Caprylic/Capric Triglyceride, Helianthus Annuus (Sunflower) Seed Wax, C12-15 Alkyl Benzoate, Jojoba Esters, Octyldodecyl Neopentanoate, Shea Butter Ethyl Esters, Tridecyl Salicylate, Euphorbia Cerifera (Candelilla) Wax, Methylpropanediol, Silica, Polyglyceryl-4 Diisostearate/Polyhydroxystearate/Sebacate, Allantoin, Caprylyl Glycol, Lecithin, Phenylpropanol, Tocopherol.

Questions?

1-866-41-AVENE (28363)

1-877-441-2011 (CAN)